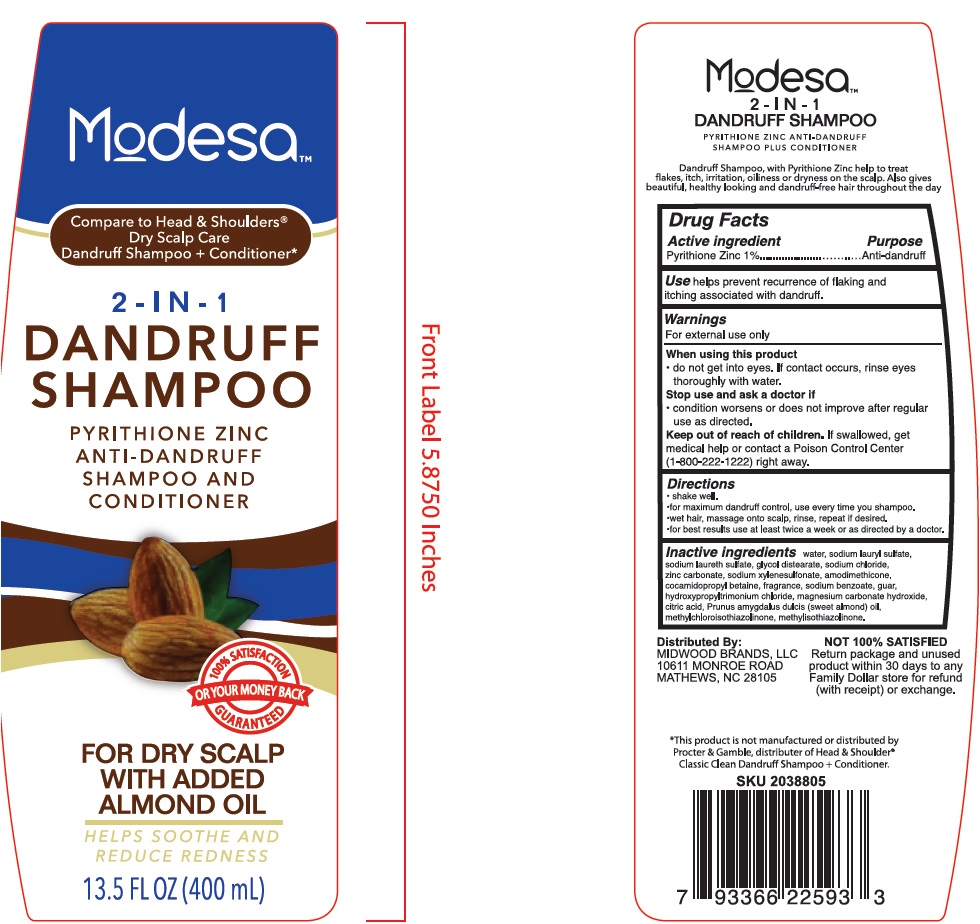 DRUG LABEL: Modesa 2 in 1 Dandruff Almond Oil Dry Scalp
NDC: 40104-432 | Form: SHAMPOO
Manufacturer: NINGBO PULISI DAILY CHEMICAL PRODUCTS CO., LTD.
Category: otc | Type: HUMAN OTC DRUG LABEL
Date: 20190402

ACTIVE INGREDIENTS: PYRITHIONE ZINC 1 g/100 g
INACTIVE INGREDIENTS: water; SODIUM LAURETH SULFATE; GLYCOL DISTEARATE; SODIUM CHLORIDE; GUAR HYDROXYPROPYLTRIMONIUM CHLORIDE (1.7 SUBSTITUENTS PER SACCHARIDE); ZINC SULFATE; DIMETHICONE; CETYL ALCOHOL; BENZYL ALCOHOL; METHYLCHLOROISOTHIAZOLINONE; METHYLISOTHIAZOLINONE; SODIUM HYDROXIDE; CITRIC ACID, 1-STEARYL ESTER; SODIUM BENZOATE; FD&C BLUE NO. 1; D&C RED NO. 33

Active Ingredient Purpose

Pyrithione Zinc 1.00% Anti-dandruff

PURPOSE

Help prevent to treat flakes, itch, irritation, oilness or dryness caused by dandruff.

KEEP OUT OF REACH OF CHILDREN

If swallowed, get medical help or contact a Poison Control Center （1-800-222-1222）right away.
Avoid contact with eyes, if contact occurs rinse eyes with plenty of water.

INDICATIONS AND USAGE

wet hair, squeeze small amount to palm, lather, rinse well for best results use at least twice a week or as directed by a doctor.

WARNINGS

For external use only.

Stop use and ask a doctor if Condition worsens or does not improve after regular use as directed.

DOSAGE AND ADMINISTRATION

small amount to palm, or as directed by a doctor.

INACTIVE INGREDIENT

water, sodium laureth sulfate, sodium lauryl sulfate, glycol distearate, sodium chloride, zinc barbonate, sodium xylenesulfonate, amodimethicone, cocamidopropyl betaine, fragrance, sodium benzoate, guar hydroxypropyltrimonium chloride, magnesium carbonate hydroxide, citric acid, prunus amygdalus dulcis (sweet almond) oil, methylchloroisothiazolinone, methylisothiazolinone.